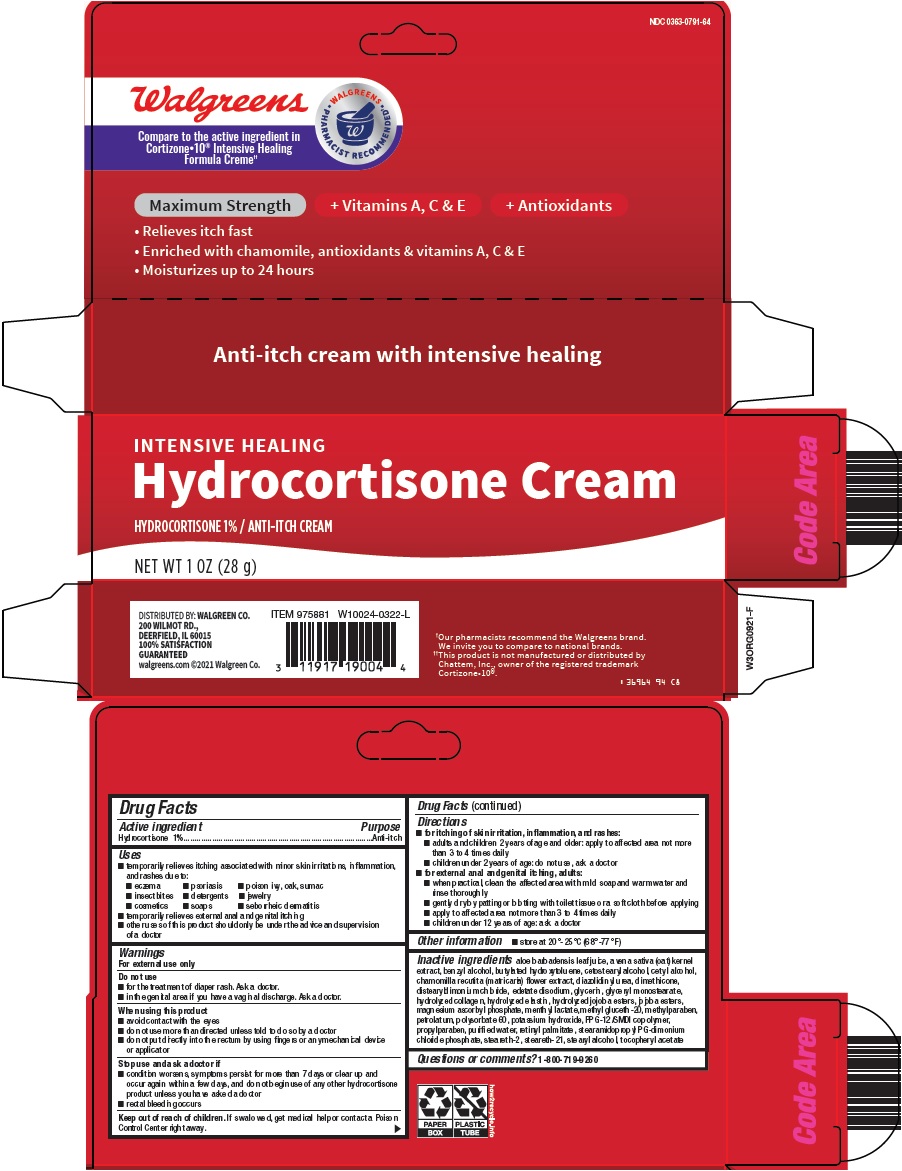 DRUG LABEL: Hydrocortisone
NDC: 0363-0791 | Form: CREAM
Manufacturer: Walgreen Company
Category: otc | Type: HUMAN OTC DRUG LABEL
Date: 20241105

ACTIVE INGREDIENTS: HYDROCORTISONE 1 g/100 g
INACTIVE INGREDIENTS: ALOE VERA LEAF; OAT; BENZYL ALCOHOL; BUTYLATED HYDROXYTOLUENE; CETOSTEARYL ALCOHOL; CETYL ALCOHOL; CHAMOMILE; DIAZOLIDINYL UREA; DIMETHICONE; DISTEARYLDIMONIUM CHLORIDE; EDETATE DISODIUM; GLYCERIN; GLYCERYL MONOSTEARATE; HYDROLYZED JOJOBA ESTERS (ACID FORM); MAGNESIUM ASCORBYL PHOSPHATE; MENTHYL LACTATE, (-)-; METHYL GLUCETH-20; METHYLPARABEN; PETROLATUM; POLYSORBATE 60; POTASSIUM HYDROXIDE; PROPYLPARABEN; WATER; VITAMIN A PALMITATE; STEARETH-2; STEARETH-21; STEARYL ALCOHOL; STEARAMIDOPROPYL PROPYLENE GLYCOL-DIMONIUM CHLORIDE PHOSPHATE; PPG-12/SMDI COPOLYMER; .ALPHA.-TOCOPHEROL ACETATE; HYDROLYZED BOVINE ELASTIN (BASE; 1000 MW)

Walgreen Co. Hydrocortisone Cream Drug Facts

Active ingredient

Hydrocortisone 1%

Purpose

Anti-itch

Uses

- temporarily relieves itching associated with minor skin irritations, inflammation, and rashes due to:
- eczema
- psoriasis
- poison ivy, oak, sumac
- insect bites
- detergents
- jewelry
- cosmetics
- soaps
- seborrheic dermatitis
- temporarily relieves external anal and genital itching
- other uses of this product should only be under the advice and supervision of a doctor

Warnings

For external use only

Do not use

- for the treatment of diaper rash. Ask a doctor.
- in the genital area if you have a vaginal discharge. Ask a doctor.

When using this product

- avoid contact with the eyes
- do not use more than directed unless told to do so by a doctor
- do not put directly into the rectum by using fingers or any mechanical device or applicator

Stop use and ask a doctor if

- condition worsens, symptoms persist for more than 7 days or clear up and occur again within a few days, and do not begin use of any other hydrocortisone product unless you have asked a doctor
- rectal bleeding occurs

Keep out of reach of children.

If swallowed, get medical help or contact a Poison Control Center right away.

Directions

- for itching of skin irritation, inflammation, and rashes:
- adults and children 2 years of age and older: apply to affected area not more than 3 to 4 times daily
- children under 2 years of age: do not use, ask a doctor
- for external anal and genital itching, adults:
- when practical, clean the affected area with mild soap and warm water and rinse thoroughly
- gently dry by patting or blotting with toilet tissue or a soft cloth before applying
- apply to affected area not more than 3 to 4 times daily
- children under 12 years of age: ask a doctor

Other information

- store at 20°-25°C (68°-77°F)

Inactive ingredients

aloe barbadensis leaf juice, avena sativa (oat) kernel extract, benzyl alcohol, butylated hydroxytoluene, cetostearyl alcohol, cetyl alcohol, chamomilla recutita (matricaria) flower extract, diazolidinyl urea, dimethicone, distearyldimonium chloride, edetate disodium, glycerin, glyceryl monostearate, hydrolyzed collagen, hydrolyzed elastin, hydrolyzed jojoba esters, jojoba esters, magnesium ascorbyl phosphate, menthyl lactate, methyl gluceth-20, methylparaben, petrolatum, polysorbate 60, potassium hydroxide, PPG-12/SMDI copolymer, propylparaben, purified water, retinyl palmitate, stearamidopropyl PG-dimonium chloride phosphate, steareth-2, steareth-21, stearyl alcohol, tocopheryl acetate

Questions or comments?

1-800-719-9260

Principal Display Panel

Walgreens

WALGREENS PHARMACIST RECOMMENDED

Compare to the active ingredient in Cortizone-10® Intensive Healing Formula Creme

Maximum Strength + Vitamins A, C & E + Antioxidants

• Relieves itch fast

• Enriched with chamomile, antioxidants & vitamins A, C & E

• Moisturizes up to 24 hours

INTENSIVE HEALING

Hydrocortisone Cream

HYDROCORTISONE 1% / ANTI-ITCH CREAM

NET WT 1 OZ (28 g)